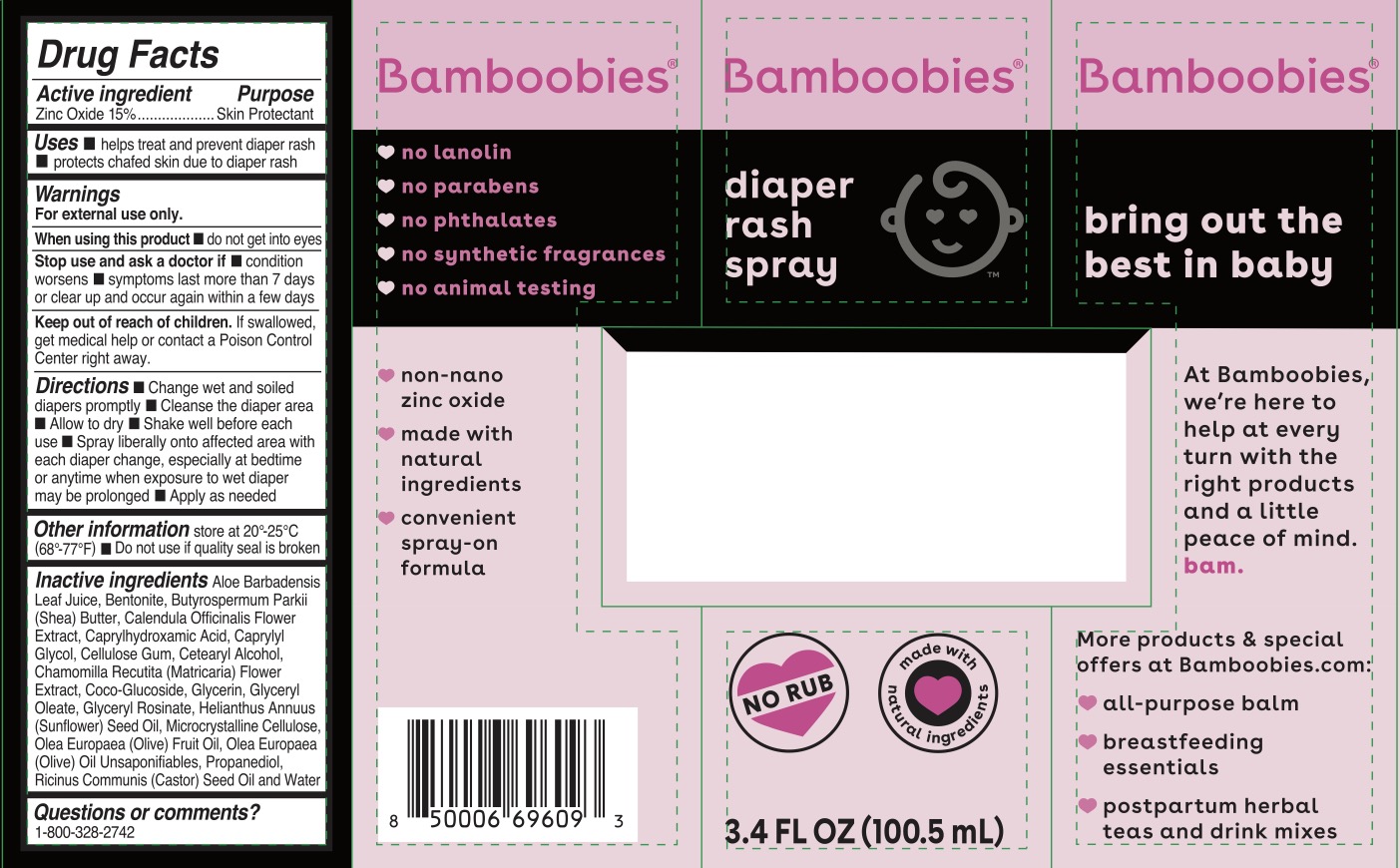 DRUG LABEL: Bamboobies Diaper Rash
NDC: 72839-132 | Form: SPRAY
Manufacturer: Derma Care Research Labs, LLC
Category: otc | Type: HUMAN OTC DRUG LABEL
Date: 20241219

ACTIVE INGREDIENTS: ZINC OXIDE 15 g/100 mL
INACTIVE INGREDIENTS: SHEA BUTTER; CAPRYLYL GLYCOL; GLYCERIN; GLYCERYL OLEATE; OLEA EUROPAEA (OLIVE) OIL UNSAPONIFIABLES; PROPANEDIOL; BENTONITE; OLIVE OIL; CAPRYLHYDROXAMIC ACID; CARBOXYMETHYLCELLULOSE SODIUM; GLYCERYL ROSINATE; WATER; CETOSTEARYL ALCOHOL; COCO GLUCOSIDE; ALOE VERA LEAF; CALENDULA OFFICINALIS FLOWER; CHAMOMILE; SUNFLOWER OIL; CASTOR OIL; MICROCRYSTALLINE CELLULOSE

ACTIVE INGREDIENT

Zinc Oxide 15%

PURPOSE

Skin Protectant

INDICATIONS AND USAGE

Helps treat and prevent diaper rash, protects chafed skin due to diaper rash.

WARNINGS

For external use only.

When using this product do not get into eyes.

Stop use and ask a doctor if condition worsens, symptoms last more than 7 days or clear up and occur again within a few days.

KEEP OUT OF REACH OF CHILDREN

If swallowed, get medical help or contact a Poison Control Center right away.

DOSAGE AND ADMINISTRATION

Change wet and soiled diapers promptly. Cleanse the diaper area. Allow to dry. Shake well before each use. Spray liberally onto affected area with each diaper change, especially at bedtime or anytime when exposure to wet diaper may be prolonged. Apply as needed.

INACTIVE INGREDIENT

Aloe Barbadensis Leaf Juice, Bentonite, Butyrospermum Parkii (Shea) Butter, Calendula Officinalis flower Extract, Caprylhydroxamic Acid, Caprylyl Glycol, Cellulose Gum, Cetearyl Alcohol, chamomilla Recutita (Matricaria) Flower Extract, Coco-Glucoside, Glycerin, Glyceryl Oleate, Glyceryl Rosinate, Helianthus Annuus (Sunflower) Seed Oil, Microcrystalline Cellulose, Olea Europaea (Olive) Fruit Oil, Olea Europaes 9Olive) Oil Unsaponifiables, Propanediol, Ricinus Communis (Castor) Seed Oil, Water.